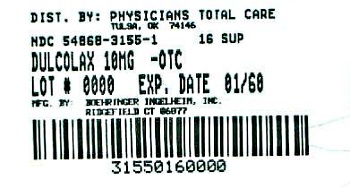 DRUG LABEL: Dulcolax
NDC: 54868-3155 | Form: SUPPOSITORY
Manufacturer: Physicians Total Care, Inc.
Category: otc | Type: HUMAN OTC DRUG LABEL
Date: 20110201

ACTIVE INGREDIENTS: bisacodyl 10 mg/1 1
INACTIVE INGREDIENTS: HYDROGENATED COCONUT OIL; HYDROGENATED PALM KERNEL OIL

Dulcolax® Suppository

Drug Facts

Active ingredient (in each suppository) | Purpose
Bisacodyl USP 10 mg .................................... | Stimulant laxative

Uses

PURPOSE

- for temporary relief of occasional constipation and irregularity
- this product generally produces bowel movement in 15 minutes to 1 hour

Warnings

For rectal use only

Ask a doctor before use if you have

- stomach pain, nausea or vomiting
- a sudden change in bowel habits that lasts more than 2 weeks

When using this product it may cause stomach discomfort, faintness, rectal burning and mild cramps

Stop use and ask a doctor if

- you have rectal bleeding or no bowel movement after using this product. These could be signs of a serious condition.
- you need to use a laxative for more than 1 week

PREGNANCY OR BREAST FEEDING

If pregnant or breast-feeding, ask a health professional before use.

Keep out of reach of children. If swallowed, get medical help or contact a Poison Control Center right away.

Directions

adults and children 12 years of age and over | 1 suppository in a single daily dose. Peel open plastic. Insert suppository well into rectum, pointed end first. Retain about 15 to 20 minutes.
children 6 to under 12 years of age | 1/2 suppository in a single daily dose
children under 2 years of age | ask a doctor

Other information

- do not store above 30°C (86°F)

Inactive ingredient

hydrogenated vegetable oil

PACKAGE LABEL

Dulcolax (bisacodyl USP) Laxative Suppositories
10 mg
NDC 54868-3155-1